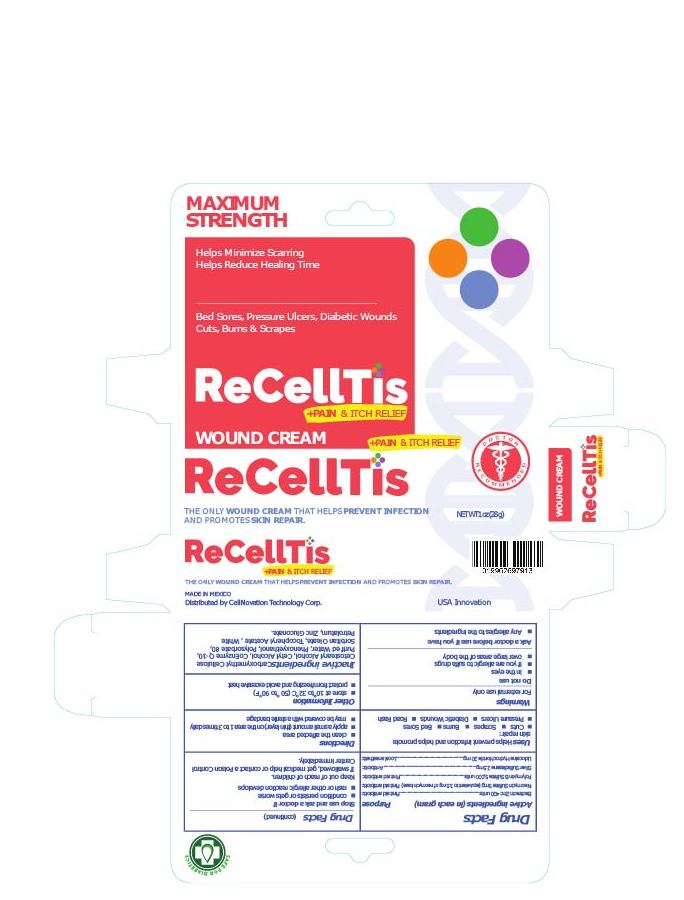 DRUG LABEL: ReCellTis
NDC: 71929-070 | Form: CREAM
Manufacturer: CellNovation Technology
Category: otc | Type: HUMAN OTC DRUG LABEL
Date: 20211206

ACTIVE INGREDIENTS: LIDOCAINE 600 mg/30 g; POLYMYXIN B SULFATE 150000 [USP'U]/30 g; BACITRACIN ZINC 12000 [USP'U]/30 g; NEOMYCIN SULFATE 105 mg/30 g
INACTIVE INGREDIENTS: SILVER 25 mg/30 g

recelltis wound 1oz tube in box

Drug Facts

Active ingredients (in each gram)

Bacitracin Zin 400 units

Neomycin Sulfate 5mg

Polymyxin B Sulfate 5,000 units

Lidocaine Hydrochloride 20mg

Uses

Helps prevent infection and helps promote skin repair:

- Cuts
- Scrapes
- Burns
- Bed Sores
- Pressure Ulcers
- Diabetic Wounds
- Road Rash

Warnings

For external use only

Do Not Use

- In the eyes
- Over large areas of the body

Ask a Doctor Before Use If You Have

- Any allergies to the ingredients

Stop Use and Ask A Doctor If

- condition persists or gets worse
- rash or other allergic reaction develops

Keep out of reach of children.

If swallowed, get medical help or contact a Poison Control Center immediately.

Directions

- clean the affected area
- apply a small amount (thin layer) on the area 1 to 3 times daily
- may be covered with a sterile bandage

Other Information

- store at 10° to 32C (50° to 90°F)
- protect from freezing and avoid excessive heat

INACTIVE INGREDIENTS

Carboxymethyl Cellulose, Cetostearyl Alcohol, Cetyl Alcohol, Coenzyme Q-10, Purified Water, Phenoxyethanol, Polysorbate 80, Sorbitan Oleate, Tocopheryl Acetate, White Petrolatum, Zinc Gluconate